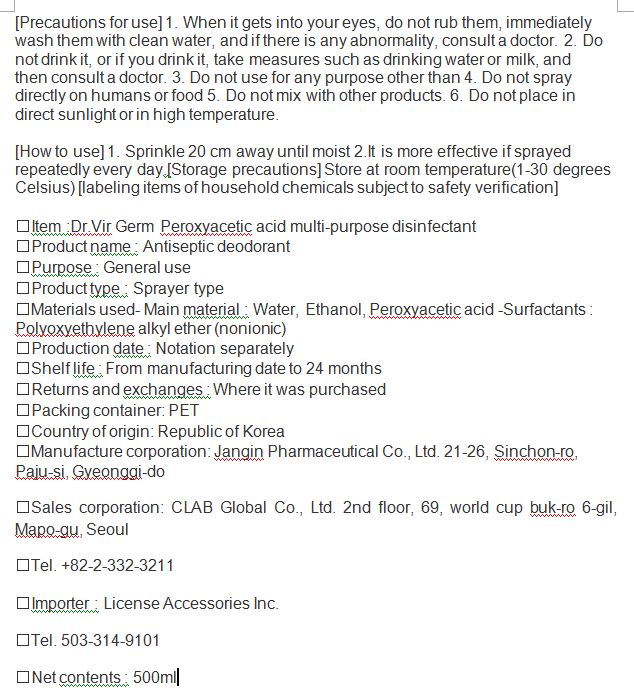 DRUG LABEL: Dr.Vir Germ Peroxyacetic acid Multi-disinfectant
NDC: 69255-900 | Form: LIQUID
Manufacturer: JANGIN PHARM CO.,LTD.
Category: otc | Type: HUMAN OTC DRUG LABEL
Date: 20200721

ACTIVE INGREDIENTS: PERACETIC ACID 5 g/100 mL
INACTIVE INGREDIENTS: PAEONIA LACTIFLORA ROOT OIL; WATER; CULTIVATED MUSHROOM; GREEN TEA LEAF; LEVOMENTHOL; ALCOHOL

ACTIVE INGREDIENT

alcohol, Peroxyacetic acid

INACTIVE INGREDIENT

Water, Surfactants : Polyoxyethylene alkyl ether (nonionic)

PURPOSE

multi disinfectant

Keep out of reach of children

INDICATIONS AND USAGE

1. Sprinkle 20 cm away until moist 2.It is more effective if sprayed repeatedly every day.[Storage precautions] Store at room temperature(1-30 degrees Celsius) [labeling items of household chemicals subject to safety verification]

WARNINGS

1. When it gets into your eyes, do not rub them, immediately wash them with clean water, and if there is any abnormality, consult a doctor.

2. Do not drink it, or if you drink it, take measures such as drinking water or milk, and

then consult a doctor.

3. Do not use for any purpose other than

4. Do not spray directly on humans or food

5. Do not mix with other products.

6. Do not place in direct sunlight or in high temperature.

DOSAGE AND ADMINISTRATION

for external use only